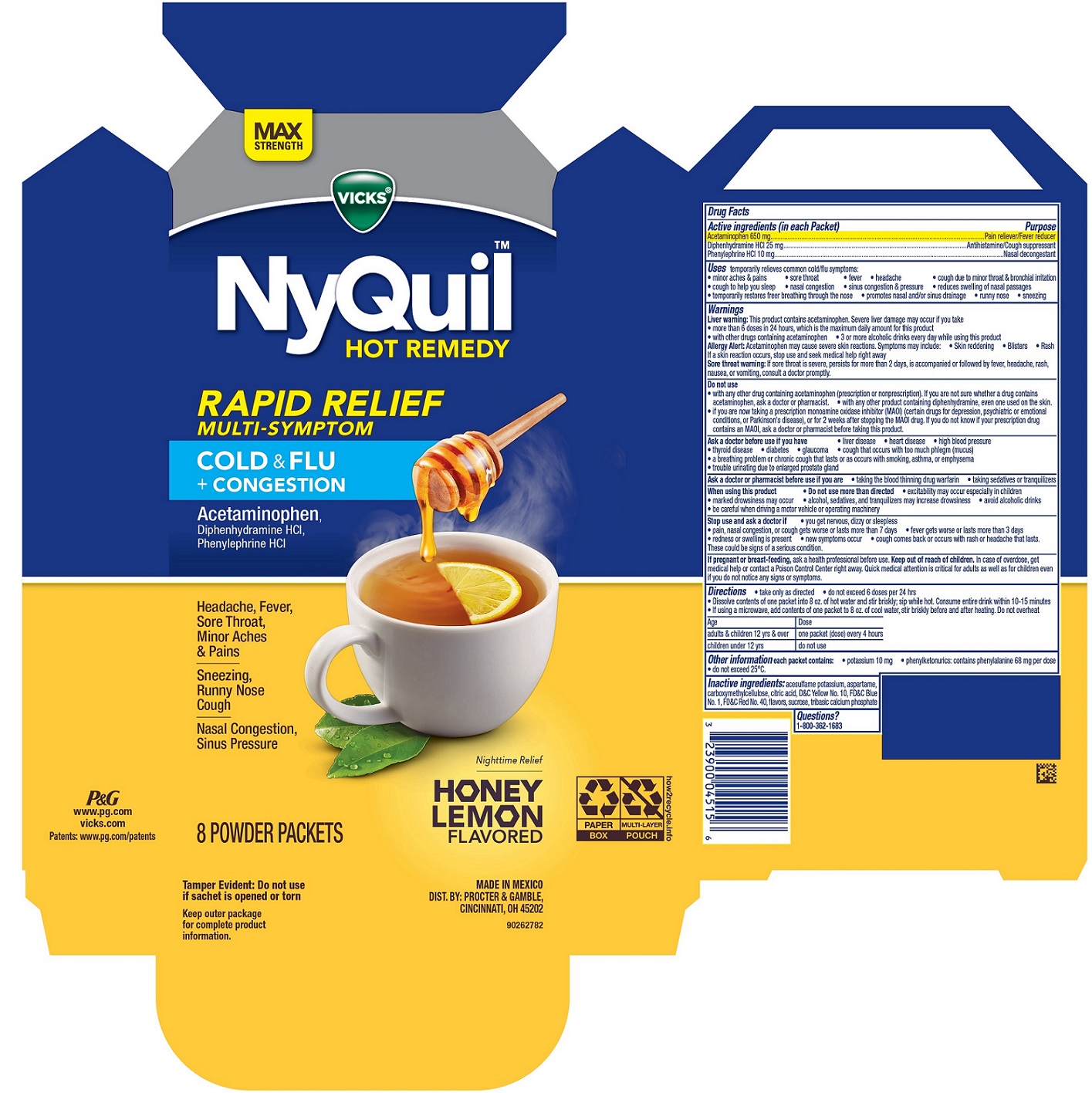 DRUG LABEL: Vicks NyQuil HOT REMEDY RAPID RELIEF MULTI-SYMPTOM
NDC: 58933-551 | Form: POWDER, FOR SOLUTION
Manufacturer: Procter & Gamble Manufactura S de RL de CV
Category: otc | Type: HUMAN OTC DRUG LABEL
Date: 20260116

ACTIVE INGREDIENTS: PHENYLEPHRINE HYDROCHLORIDE 10 mg/5 g; ACETAMINOPHEN 650 mg/5 g; DIPHENHYDRAMINE HYDROCHLORIDE 25 mg/5 g
INACTIVE INGREDIENTS: D&C YELLOW NO. 10; FD&C BLUE NO. 1; ASPARTAME; SUCROSE; FD&C RED NO. 40; TRIBASIC CALCIUM PHOSPHATE; CITRIC ACID MONOHYDRATE; ACESULFAME POTASSIUM; CARBOXYMETHYLCELLULOSE

Vicks® NyQuil™ HOT REMEDY
RAPID RELIEF
MULTI-SYMPTOM
COLD & FLU PLUS CONGESTION

Drug Facts

Active Ingredient (in each Packet)

Acetaminophen650 mg

Diphenhydramine HCl 25 mg

Phenylephrine HCl 10 mg

Purpose

Pain reliever/fever reducer

Antihistamine, Cough Suppressant

Nasal decongestant

Uses

temporarily relieves common cold/flu symptoms:

- minor aches & pains
- sore throat
- fever
- headache
- cough due to minor throat & bronchial irritation
- cough to help you sleep
- nasal congestion
- sinus congestion & pressure
- reduces swelling of nasal passages
- temporarily restores freer breathing through the nose
- promotes nasal and/or sinus drainage
- runny nose
- sneezing

Warnings

Liver warning:

This product contains acetaminophen. Severe liver damage may occur if you take

- more than 6 doses in 24 hours, which is the maximum daily amount for this product
- with other drugs containing acetaminophen
- 3 or more alcoholic drinks every day while using this product

Allergy Alert:

Acetaminophen may cause severe skin reactions. Symptoms may include:

- Skin reddening
- Blisters
- Rash

If a skin reaction occurs, stop use and seek medical help right away

Sore throat warning:

If sore throat is severe, persists for more than 2 days, is accompanied or followed by fever, headache, rash, nausea, or vomiting, consult a doctor promptly.

Ask a doctor before use if you have

- liver disease
- heart disease
- high blood pressure
- thyroid disease
- diabetes
- glaucoma
- cough that occurs with too much phlegm (mucus)
- a breathing problem or chronic cough that lasts or as occurs with smoking, asthma, or emphysema
- trouble urinating due to enlarged prostate gland

Do not use

- with any other drug containing acetaminophen (prescription or nonprescription). If you are not sure whether a drug contains acetaminophen, ask a doctor or pharmacist.
- with any other product containing diphenhydramine, even one used on the skin.
- if you are now taking a prescription monoamine oxidase inhibitor (MAOI) (certain drugs for depression, psychiatric or emotional conditions, or Parkinson's disease), or for 2 weeks after stopping the MAOI drug. If you do not know if your prescription drug contains an MAOI, ask a doctor or pharmacist before taking this product.

Ask a doctor or pharmacist before use if you are

- taking the blood thinning drug warfarin
- taking sedatives or tranquilizers

When using this product

- Do not use more than directed
- excitability may occur especially in children
- marked drowsiness may occur
- alcohol, sedatives, and tranquilizers may increase drowsiness
- avoid alcoholic drinks
- be careful when driving a motor vehicle or operating machinery

Stop use and ask a doctor if

- you get nervous, dizzy or sleepless
- pain, nasal congestion, or cough gets worse or lasts more than 7 days
- fever gets worse or lasts more than 3 days
- redness or swelling is present
- new symptoms occur
- cough comes back or occurs with rash or headache that lasts.

These could be signs of a serious condition.

If pregnant or breast-feeding,

ask a health professional before use.

Keep out of reach of children.

OVERDOSAGE

In case of overdose, get medical help or contact a Poison Control Center right away. Quick medical attention is critical for adults as well as for children even if you do not notice any signs or symptoms.

Directions

• take only as directed

• do not exceed 6 doses per 24 hrs

• Dissolve contents of one packet into 8 oz. of hot water and stir briskly; sip while hot. Consume entire drink within 10-15 minutes

• If using a microwave, add contents of one packet to 8 oz. of cool water, stir briskly before and after heating. Do not overheat

Age | Dose
Adults & children 12 yrs & over | one packet (dose) every 4 hours
Children under 12 yrs | Do not use

Other information

• each packet contains:potassium 10 mg

• phenylketonurics: contains phenylalanine 68 mg per dose

• do not exceed 25°C.

Inactive ingredients

acesulfame potassium, aspartame, carboxymethylcellulose, citric acid, D&C Yellow No. 10, FD&C Blue No. 1, FD&C Red No. 40, flavors, sucrose, tribasic calcium phosphate

Questions?

1-800-362-1683

Tamper Evident: Do not use if sachet is opened or torn

Keep outer package for complete product information.

MADE IN MEXICO

DIST. BY PROCTER & GAMBLE,
CINCINNATI OH 45202

PRINCIPAL DISPLAY PANEL - 8 packet package

MAX STRENGTH

Vicks® NyQuil™ HOT REMEDY

RAPID RELIEF MULTI-SYMPTOM

COLD & FLU + CONGESTION

Acetaminophen, Diphenhydramine HCl, Phenylephrine HCl

Headache, Fever, Sore Throat, Minor Aches & Pains

Sneezing, Runny Nose, Cough

Nasal Congestion, Sinus Pressure

Nighttime Relief

HONEY LEMON FLAVORED

8 POWDER PACKETS